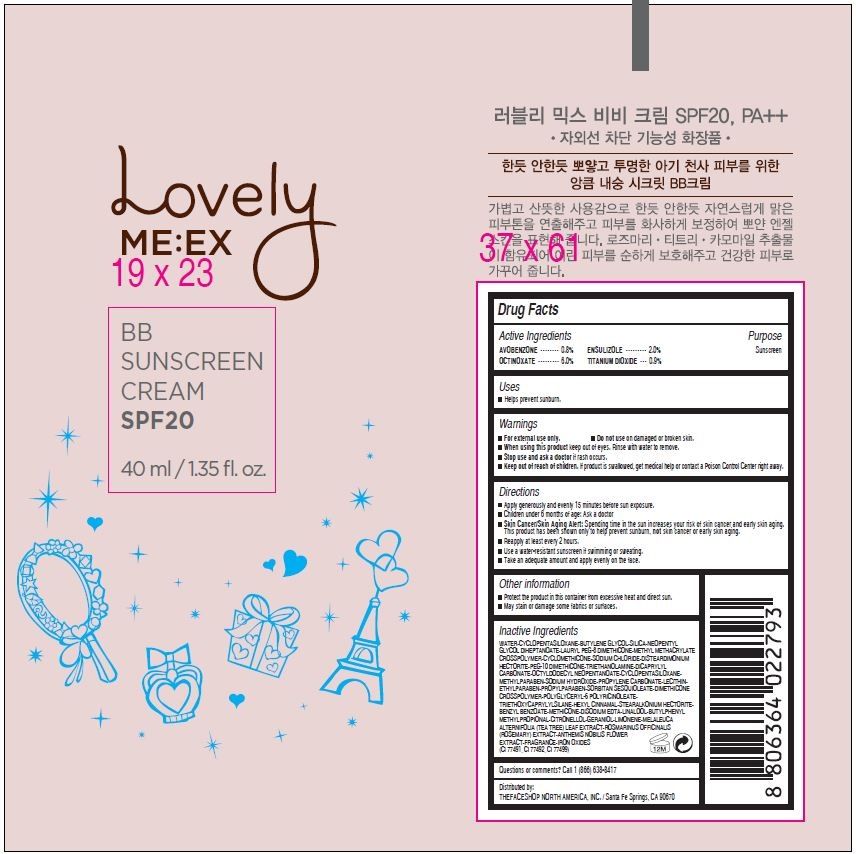 DRUG LABEL: LOVELY ME EX
NDC: 51523-042 | Form: CREAM
Manufacturer: THEFACESHOP CO., LTD.
Category: otc | Type: HUMAN OTC DRUG LABEL
Date: 20141120

ACTIVE INGREDIENTS: OCTINOXATE 2.4 g/40 mL; ENSULIZOLE 0.8 g/40 mL; AVOBENZONE 0.32 g/40 mL; TITANIUM DIOXIDE 0.36 g/40 mL
INACTIVE INGREDIENTS: WATER

Active Ingredients

AVOBENZONE • • • • • • • • 0.8% ENSULIZOLE • • • • • • • • • 2.0%
OCTINOXATE • • • • • • • • • 6.0% TITANIUM DIOXIDE • • • 0.9%

Purpose

Sunscreen

Sunscreen

Sunscreen

Sunscreen

Warnings

For external use only.

Do not use on damaged or broken skin

When using this product keep out of eyes. Rinse with water to remove.

Stop use and ask a doctor if rash occurs.

Keep out of reach of children.

If product is swallowed, get medical help or contact a Poison Control Center right away.

Directions

Apply generously and evenly 15 minutes before sun exposure.
Children under 6 months of age: Ask a doctor
Skin Cancer/Skin Aging Alert: Spending time in the sun increases your risk of skin cancer and early skin aging.
This product has been shown only to help prevent sunburn, not skin cancer or early skin aging.
Reapply at least every 2 hours.
Use a water-resistant sunscreen if swimming or sweating.
Take an adequate amount and apply evenly on the face.

Other information

Protect the product in this container from excessive heat and direct sun.
May stain or damage some fabrics or surfaces

Inactive Ingredients

WATER•CYCLOPENTASILOXANE•BUTYLENE GLYCOL•SILICA•NEOPENTYL
GLYCOL DIHEPTANOATE•LAURYL PEG-8 DIMETHICONE•METHYL METHACRYLATE
CROSSPOLYMER•CYCLOMETHICONE•SODIUM CHLORIDE•DISTEARDIMONIUM
HECTORITE•PEG-10 DIMETHICONE•TRIETHANOLAMINE•DICAPRYLYL
CARBONATE•OCTYLDODECYL NEOPENTANOATE•CYCLOPENTASILOXANE•
METHYLPARABEN•SODIUM HYDROXIDE•PROPYLENE CARBONATE•LECITHIN•
ETHYLPARABEN•PROPYLPARABEN•SORBITAN SESQUIOLEATE•DIMETHICONE
CROSSPOLYMER•POLYGLYCERYL-6 POLYRICINOLEATE•
TRIETHOXYCAPRYLYLSILANE•HEXYL CINNAMAL•STEARALKONIUM HECTORITE•
BENZYL BENZOATE•METHICONE•DISODIUM EDTA•LINALOOL•BUTYLPHENYL
METHYLPROPIONAL•CITRONELLOL•GERANIOL•LIMONENE•MELALEUCA
ALTERNIFOLIA (TEA TREE) LEAF EXTRACT•ROSMARINUS OFFICINALIS
(ROSEMARY) EXTRACT•ANTHEMIS NOBILIS FLOWER
EXTRACT•FRAGRANCE•IRON OXIDES
(CI 77491, CI 77492, CI 77499)

Questions or comments? Call 1 (866) 638-8417

Distributed by:

THEFACESHOP NORTH AMERICA, INC. / Santa Fe Springs, CA 90670

PACKAGE LABEL

Lovely ME: EX

BB SUNSCREEN CREAM

SPF20